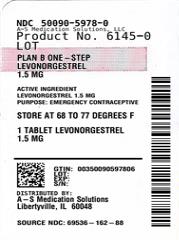 DRUG LABEL: Plan B One-Step
NDC: 50090-5978 | Form: TABLET
Manufacturer: A-S Medication Solutions
Category: otc | Type: HUMAN OTC DRUG LABEL
Date: 20231024

ACTIVE INGREDIENTS: LEVONORGESTREL 1.5 mg/1 1
INACTIVE INGREDIENTS: SILICON DIOXIDE; STARCH, POTATO; MAGNESIUM STEARATE; TALC; STARCH, CORN; LACTOSE MONOHYDRATE

Plan B One-Step®

Drug Facts

Active ingredient

Levonorgestrel 1.5 mg

Purpose

Emergency contraceptive

Use

for women to reduce chance of pregnancy after unprotected sex (if a contraceptive failed or if you did not use birth control)

Warnings

Allergy alert

Do not use if you have ever had an allergic reaction to levonorgestrel

Sexually transmitted diseases (STDs) alert

This product does not protect against HIV/AIDS or other STDs

Do not use

- if you are already pregnant (because it will not work)
- for regular birth control

Ask a doctor or pharmacist before use if you are taking efavirenz (HIV medication) or rifampin (tuberculosis treatment) or medication for seizures (epilepsy). These medications may reduce the effectiveness of levonorgestrel.

When using this product you may have

- menstrual changes
- tiredness
- breast pain
- nausea
- headache
- vomiting
- lower stomach (abdominal) pain
- dizziness

Keep out of reach of children. In case of overdose, get medical help or contact a Poison Control center right away.

Directions

- take as soon as possible within 72 hours (3 days) after unprotected sex. The sooner you take it the better it will work.
- if you vomit within 2 hours after taking the medication, call a healthcare professional to find out if you should repeat the dose

Other information

- read the instructions, warnings and enclosed product leaflet before use
- do not use if carton is open or tear strip is removed or blister seal is broken or missing
- store at 20-25°C (68-77°F)

Inactive ingredients

colloidal silicon dioxide, corn starch, lactose monohydrate, magnesium stearate, potato starch, talc

Questions?

Call 1-800-330-1271 or visit www.PlanBOneStep.com

Distributed by:
Foundation Consumer Healthcare, LLC. (FCH)
Pittsburgh, PA 15205

HOW SUPPLIED

Product: 50090-5978

NDC: 50090-5978-0 1 TABLET in a BLISTER PACK / 1 in a BOX, UNIT-DOSE